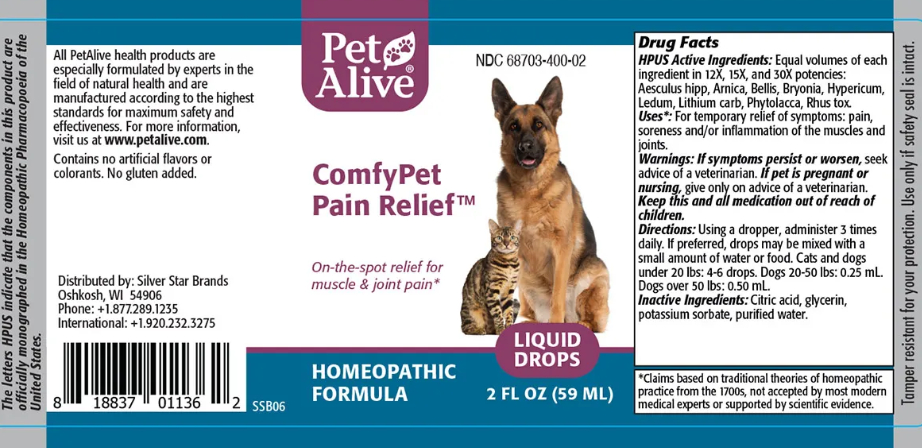 DRUG LABEL: PetAlive ComfyPet Pain Relief
NDC: 68703-400 | Form: LIQUID
Manufacturer: SILVER STAR BRANDS
Category: homeopathic | Type: OTC ANIMAL DRUG LABEL
Date: 20251216

ACTIVE INGREDIENTS: HORSE CHESTNUT 12 [hp_X]/59 mL; ARNICA MONTANA 12 [hp_X]/59 mL; BELLIS PERENNIS 12 [hp_X]/59 mL; BRYONIA ALBA ROOT 12 [hp_X]/59 mL; HYPERICUM PERFORATUM 12 [hp_X]/59 mL; LEDUM PALUSTRE TWIG 12 [hp_X]/59 mL; LITHIUM CARBONATE 12 [hp_X]/59 mL; PHYTOLACCA AMERICANA ROOT 12 [hp_X]/59 mL; TOXICODENDRON PUBESCENS LEAF  12 [hp_X]/59 mL
INACTIVE INGREDIENTS: CITRIC ACID MONOHYDRATE; GLYCERIN; POTASSIUM SORBATE; WATER

ComfyPet Pain Relief

PURPOSE

On-the-spot relief for muscle and joint pain

ACTIVE INGREDIENT

HPUS Active Ingredients: Equal volumes of each ingredient in 12X, 15X, and 30X potencies:

Aesculus hipp

Arnica

Bellis

Bryonia

Hypericum

Ledum

Lithium carb

Phytolacca

Rhus tox

INDICATIONS AND USAGE

Uses: For temporary relief of symptoms: pain, soreness and/or inflammation of the muscles and joints.

WARNINGS

Warnings: If symptoms persist or worsen, seek advice of a veterinarian.

PREGNANCY OR BREAST FEEDING

If pet is pregnant or nursing, give only on advice of a veterinarian

KEEP OUT OF REACH OF CHILDREN

Keep this and all medication out of reach of children.

DOSAGE AND ADMINISTRATION

Directions: Using a dropper, administer 3 times daily. If preferred, drops may be mixed with a small amount of water or food. Cats and dogs under 20 lbs: 4-6 drops. Dogs 20-50 lbs: 0.25 mL. Dogs over 50 lbs: 0.50 mL.

INACTIVE INGREDIENT

Inactive Ingredients: Citric acid, glycerin, potassium sorbate, purified water.

INFORMATION FOR OWNERS/CAREGIVERS

The letters HPUS indicate that the components in this product are officially monographed in the Homeopathic Pharmacopoeia of the United States

All PetAlive health products are especially formulated by experts in the field of natural health and are manufactured according to the highest standards for maximum safety and effectiveness. For more information, visit us at www.petalive.com.

Contains no artificial flavors or colorants. No gluten added.

Distributed by: Silver Star Brands
Oshkosh, WI 54906
Phone: +1.877.289.1235
International: +1.920.232.3275

STORAGE AND HANDLING

Tamper resistant for your protection. Use only if safety seal is intact